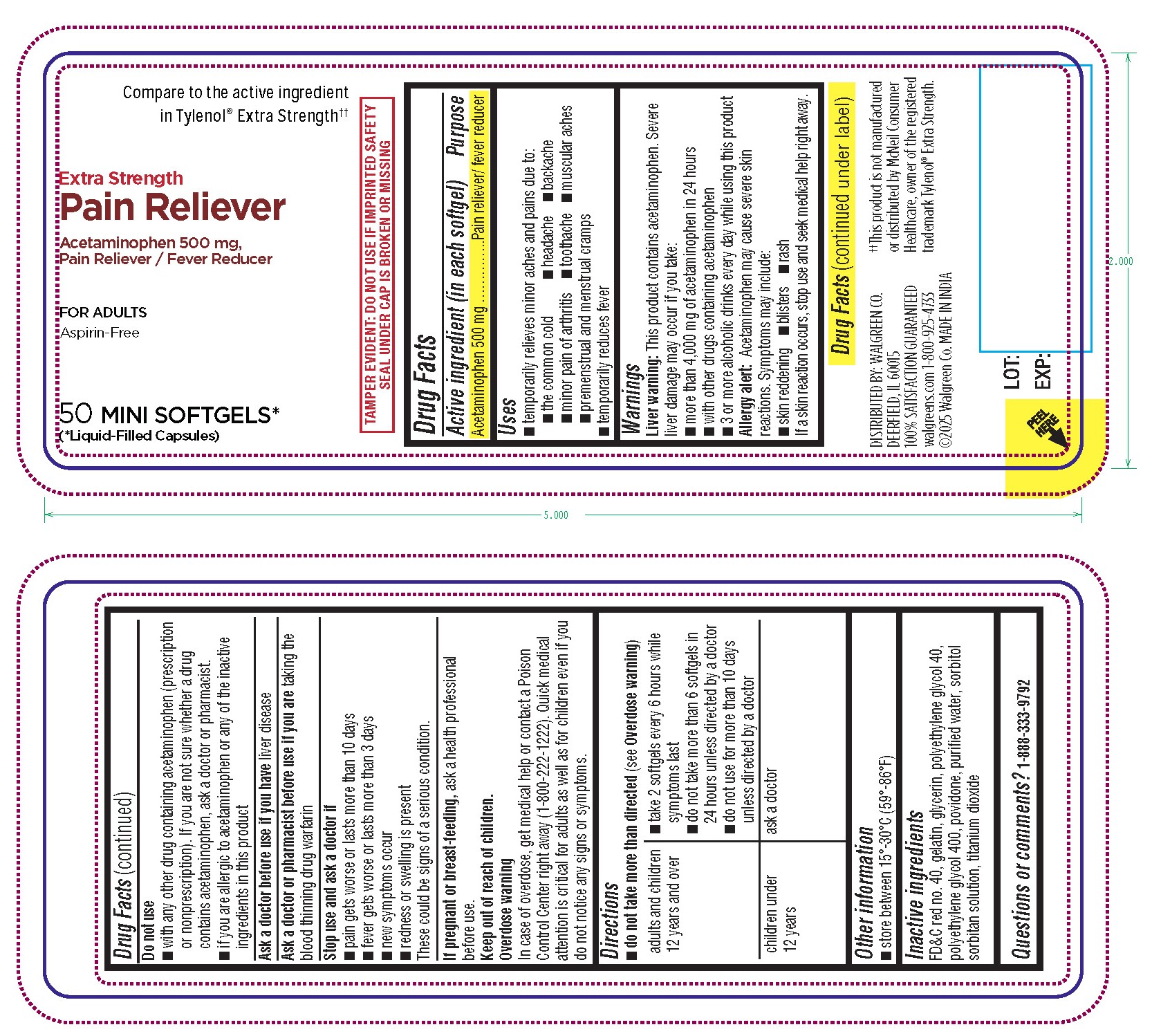 DRUG LABEL: Pain Reliever
NDC: 0363-6684 | Form: CAPSULE, LIQUID FILLED
Manufacturer: Walgreens
Category: otc | Type: HUMAN OTC DRUG LABEL
Date: 20251231

ACTIVE INGREDIENTS: ACETAMINOPHEN 500 mg/1 1
INACTIVE INGREDIENTS: POLYETHYLENE GLYCOL, UNSPECIFIED; POVIDONE; GELATIN; TITANIUM DIOXIDE; WATER; SORBITOL; FD&C RED NO. 40; POLYETHYLENE GLYCOL 400; GLYCERIN

Pain Reliever 500mg (Minis-red opaque)

Drug Facts

Active ingredient (in each softgelatin capsule)

Acetaminophen 500mg

Purpose

Pain reliever/fever reducer

Uses

- temporarily relieves minor aches and pains due to:
- the common cold
- headache
- backache
- minor pain of arthritis
- toothache
- muscular aches
- premenstrual and menstrual cramps
- temporarily reduces fever

Warnings

Liver warning: This product contains acetaminophen.Severe liver damage may occur if you take:
• more than 4,000 mg of acetaminophen in 24 hours
• with other drugs containing acetaminophen
• 3 or more alcoholic drinks every day while using this product

Allergy alert: acetaminophen may cause severe skin reactions. Symptoms may include:
• skin reddening
• blisters
• rash
If a skin reaction occurs, stop use and seek medical help right away.

Do not use
• with any other drug containing acetaminophen (prescription or nonprescription). If you are not sure whether a drug contains acetaminophen, ask a doctor or pharmacist.
• if you are allergic to acetaminophen or any of the inactive ingredients in this product.

Ask a doctor before use if youhave liver disease

Ask a doctor or pharmacist before use if youare taking the blood thinning drug warfarin

Stop use and ask a doctor if
• pain gets worse or lasts more than 10 days
• fever gets worse or lasts more than 3 days
• new symptoms occur
• redness or swelling is present
These could be signs of a serious condition.

PREGNANCY OR BREAST FEEDING

If pregnant or breast-feeding, ask a health professional before use.

Keep out of reach of children.

OVERDOSAGE

Overdose Warning

In case of overdose, get medical help or contact a Poison Control Center right away (1-800-222-1222). Quick medical attention is for critical for adults as well as for children even if you do not notice any signs or symptoms.

Direction

Do not take more than directed (see Overdose warning)

adults and children 12 yeards and over | - take 2 softgels every 6 hours while symptoms last - do not take more than 6 softgels in 24 hours unless directed by a doctor - do not use for more than 10 days unless directed by a doctor
children under 12 years | ask a doctor

Other Information

- store between 15°-30°C (59°-86°F)

Inactive ingredients

FD&C red no.40, gelatin, glycerin, polyethylene glycol 40 ,polyethylene glycol 400, povidone, purified water, sorbitol sorbitan solution, titanium dioxide

Questions or comments?1-888-333-9792